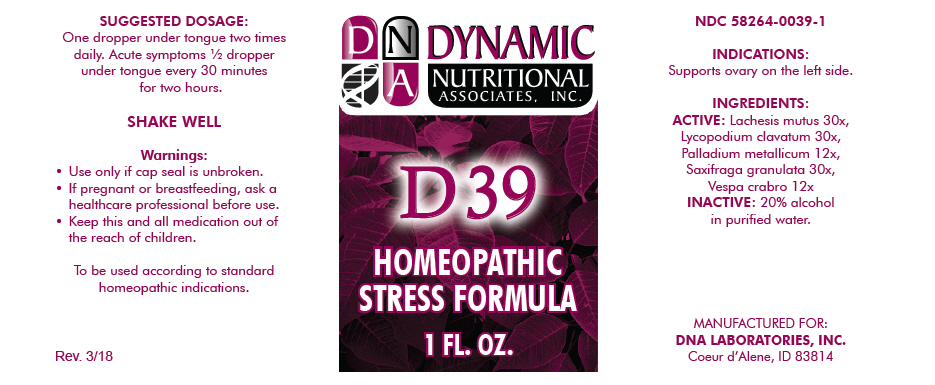 DRUG LABEL: D-39
NDC: 58264-0039 | Form: SOLUTION
Manufacturer: DNA Labs, Inc.
Category: homeopathic | Type: HUMAN OTC DRUG LABEL
Date: 20250113

ACTIVE INGREDIENTS: LACHESIS MUTA VENOM 30 [hp_X]/1 mL; LYCOPODIUM CLAVATUM SPORE 30 [hp_X]/1 mL; PALLADIUM 12 [hp_X]/1 mL; SAXIFRAGA GRANULATA WHOLE 30 [hp_X]/1 mL; VESPA CRABRO 12 [hp_X]/1 mL
INACTIVE INGREDIENTS: ALCOHOL; WATER

D-39

NDC 58264-0039-1

INDICATIONS

PURPOSE

Supports ovary on the left side.

INGREDIENTS

ACTIVE

Lachesis mutus 30x, Lycopodium clavatum 30x, Palladium metallicum 12x, Saxifraga granulata 30x, Vespa crabro 12x

INACTIVE

20% alcohol in purified water.

SUGGESTED DOSAGE

One dropper under tongue two times daily. Acute symptoms ½ dropper under tongue every 30 minutes for two hours.

STORAGE AND HANDLING

SHAKE WELL

Warnings

- Use only if cap seal is unbroken.

PREGNANCY OR BREAST FEEDING

- If pregnant or breastfeeding, ask a healthcare professional before use.

KEEP OUT OF REACH OF CHILDREN

- Keep this and all medication out of the reach of children.

To be used according to standard homeopathic indications.

PRINCIPAL DISPLAY PANEL - 1 FL. OZ. Bottle Label

DYNAMIC
NUTRITIONAL
ASSOCIATES, INC.

D 39

HOMEOPATHIC
STRESS FORMULA

1 FL. OZ.